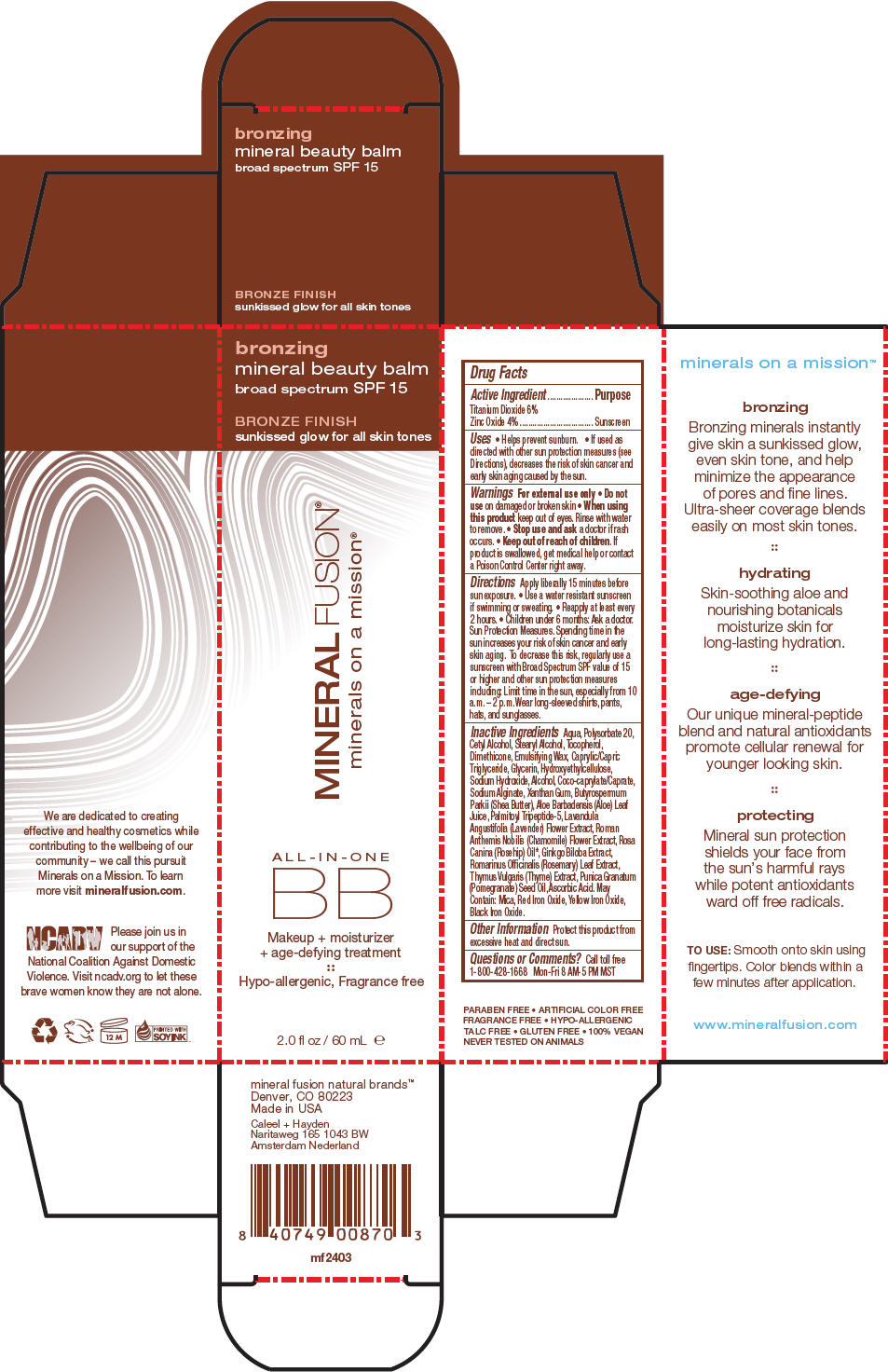 DRUG LABEL: BRONZING MINERAL BEAUTY BALM SPF 15
NDC: 55789-2403 | Form: CREAM
Manufacturer: Mineral Fusion Natural Brands
Category: otc | Type: HUMAN OTC DRUG LABEL
Date: 20150828

ACTIVE INGREDIENTS: TITANIUM DIOXIDE 3.6 g/60 mL; ZINC OXIDE 2.4 g/60 mL
INACTIVE INGREDIENTS: WATER 42 mL/60 mL; POLYSORBATE 20; CETYL ALCOHOL; STEARYL ALCOHOL; TOCOPHEROL; DIMETHICONE; MEDIUM-CHAIN TRIGLYCERIDES; GLYCERIN; HYDROXYETHYL CELLULOSE (3000 MPA.S AT 1%); SODIUM HYDROXIDE; ALCOHOL; COCO-CAPRYLATE/CAPRATE; SODIUM ALGINATE; XANTHAN GUM; SHEA BUTTER; ALOE VERA LEAF; PALMITOYL TRIPEPTIDE-5; LAVANDULA ANGUSTIFOLIA FLOWER; CHAMAEMELUM NOBILE FLOWER OIL; ROSA CANINA FLOWER OIL; GINKGO; ROSEMARY OIL; THYME; POMEGRANATE SEED OIL; ASCORBIC ACID

BRONZING MINERAL BEAUTY BALM SPF 15

Drug Facts

Active Ingredient

Titanium Dioxide 6%
Zinc Oxide 4%

Purpose

Sunscreen

Uses

- Helps prevent sunburn.
- If used as directed with other sun protection measures (see Directions), decreases the risk of skin cancer and early skin aging caused by the sun.

Warnings

For external use only

- Do not use on damaged or broken skin

- When using this product keep out of eyes. Rinse with water to remove.

- Stop use and ask a doctor if rash occurs.

- Keep out of reach of children. If product is swallowed, get medical help or contact a Poison Control Center right away.

Directions

Apply liberally 15 minutes before sun exposure.

- Use a water resistant sunscreen if swimming or sweating.
- Reapply at least every 2 hours.
- Children under 6 months: Ask a doctor.

Sun Protection Measures. Spending time in the sun increases your risk of skin cancer and early skin aging. To decrease this risk, regularly use a sunscreen with Broad Spectrum SPF value of 15 or higher and other sun protection measures including: Limit time in the sun, especially from 10 a.m. – 2 p.m. Wear long-sleeved shirts, pants, hats, and sunglasses.

Inactive Ingredients

Aqua, Polysorbate 20, Cetyl Alcohol, Stearyl Alcohol, Tocopherol, Dimethicone, Emulsifying Wax, Caprylic/Capric Triglyceride, Glycerin, Hydroxyethylcellulose, Sodium Hydroxide, Alcohol, Coco-caprylate/Caprate, Sodium Alginate, Xanthan Gum, Butyrospermum Parkii (Shea Butter), Aloe Barbadensis (Aloe) Leaf Juice, Palmitoyl Tripeptide-5, Lavandula Angustifolia (Lavender) Flower Extract, Roman Anthemis Nobilis (Chamomile) Flower Extract, Rosa Canina (Rosehip) Oil*, Ginkgo Biloba Extract, Romarinus Officinalis (Rosemary) Leaf Extract, Thymus Vulgaris (Thyme) Extract, Punica Granatum (Pomegranate) Seed Oil, Ascorbic Acid. May Contain: Mica, Red Iron Oxide, Yellow Iron Oxide, Black Iron Oxide.

Other Information

Protect this product from excessive heat and direct sun.

Questions or Comments?

Call toll free 1-800-428-1668 Mon-Fri 8 AM-5 PM MST

PRINCIPAL DISPLAY PANEL - 60 mL Tube Carton

bronzing
mineral beauty balm
broad spectrum SPF 15

BRONZE FINISH
sunkissed glow for all skin tones

MINERAL FUSION®
minerals on a mission®

ALL-IN-ONE
BB

Makeup + moisturizer
+ age-defying treatment

Hypo-allergenic, Fragrance free

2.0 fl oz / 60 mL e